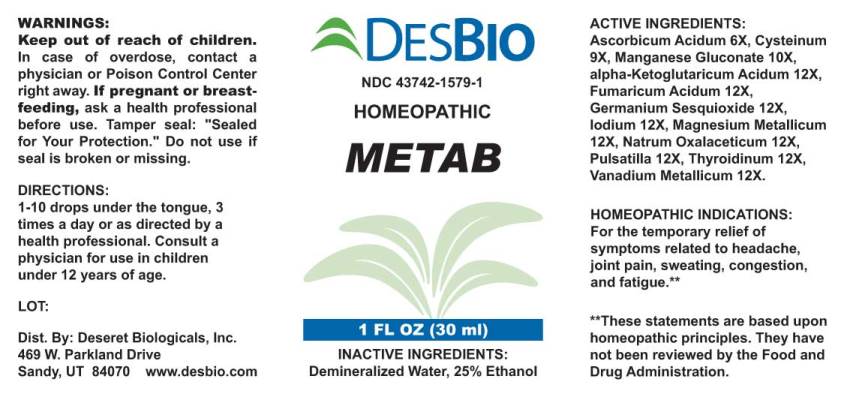 DRUG LABEL: Metab
NDC: 43742-1579 | Form: LIQUID
Manufacturer: Deseret Biologicals, Inc
Category: homeopathic | Type: HUMAN OTC DRUG LABEL
Date: 20230112

ACTIVE INGREDIENTS: ASCORBIC ACID 6 [hp_X]/1 mL; CYSTEINE 9 [hp_X]/1 mL; MANGANESE GLUCONATE 10 [hp_X]/1 mL; OXOGLURIC ACID 12 [hp_X]/1 mL; FUMARIC ACID 12 [hp_X]/1 mL; GERMANIUM SESQUIOXIDE 12 [hp_X]/1 mL; IODINE 12 [hp_X]/1 mL; MAGNESIUM 12 [hp_X]/1 mL; SODIUM DIETHYL OXALACETATE 12 [hp_X]/1 mL; ANEMONE PRATENSIS 12 [hp_X]/1 mL; SUS SCROFA THYROID 12 [hp_X]/1 mL; VANADIUM 12 [hp_X]/1 mL
INACTIVE INGREDIENTS: WATER; ALCOHOL

Drug Facts:

ACTIVE INGREDIENTS:

Ascorbicum Acidum 6X, Cysteinum 9X, Manganese Gluconate 10X, Alpha-Ketoglutaricum Acidum 12X, Fumaricum Acidum 12X, Germanium Sesquioxide 12X, Iodium 12X, Magnesium Metallicum 12X, Natrum Oxalaceticum 12X, Pulsatilla (Pratensis) 12X, Thyroidinum (Suis) 12X, Vanadium Metallicum 12X.

HOMEOPATHIC INDICATIONS:

For the temporary relief of symptoms related to headache, joint pain, sweating, congestion, and fatigue.**

**These statements are based upon traditional homeopathic principles. They have not been reviewed by the Food and Drug Administration.

WARNINGS:

Keep out of reach of children. In case of overdose, contact physician or a Poison Control Center right away.

If pregnant of breast-feeding, seek advice of a health professional before use.

Tamper seal: "Sealed for Your Protection." Do not use if seal is broken or missing.

Keep out of reach of children. In case of overdose, contact physician or a Poison Control Center right away.

DIRECTIONS:

1-10 drops under the tongue, 3 times a day or as directed by a health professional. Consult a physician for use in children under 12 years of age.

HOMEOPATHIC INDICATIONS:

For the temporary relief of symptoms related to headache, joint pain, sweating, congestion, and fatigue.**

**These statements are based upon traditional homeopathic principles. They have not been reviewed by the Food and Drug Administration.

INACTIVE INGREDIENTS:

Demineralized Water, 25% Ethanol.

QUESTIONS:

Dist. By: Deseret Biologicals, Inc.

469 W. Parkland Drive

Sandy, UT 84070 www.desbio.com

PACKAGE LABEL DISPLAY:

DESBIO
NDC 43742-1579-1
HOMEOPATHIC
METAB
1 FL OZ (30 ml)